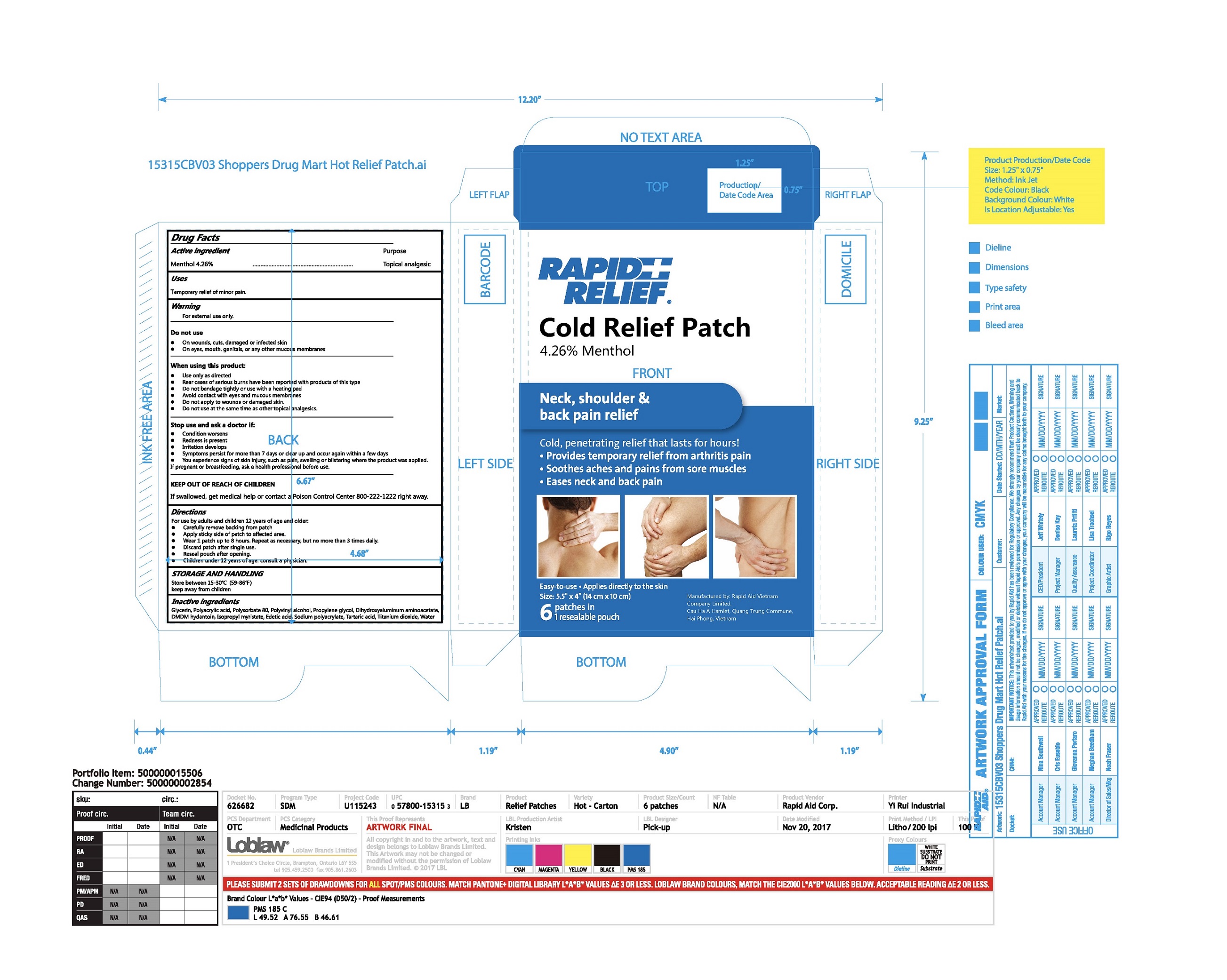 DRUG LABEL: Rapid Relief Cold Relief Patch
NDC: 83569-001 | Form: PATCH
Manufacturer: RAPID AID VIET NAM CO., LTD
Category: otc | Type: HUMAN OTC DRUG LABEL
Date: 20251016

ACTIVE INGREDIENTS: MENTHOL 4.26 g/100 g
INACTIVE INGREDIENTS: DIHYDROXYALUMINUM AMINOACETATE; ISOPROPYL MYRISTATE; TARTARIC ACID; TITANIUM DIOXIDE; POLYSORBATE 80; POLYACRYLIC ACID (450000 MW); POLYVINYL ALCOHOL, UNSPECIFIED; PROPYLENE GLYCOL; GLYCERIN; WATER; DMDM HYDANTOIN; EDETIC ACID; SODIUM POLYACRYLATE (8000 MW)

Active Ingredient(s)

Menthol 4.26% w/w

Purpose

Topical analgesic

Use

Temporary relief of minor pain.

Warnings

For external use only.

Do not use

 On wounds, cuts, damaged or infected skin
 On eyes, mouth, genitals, or any other mucous membranes

When using this product:

 Use only as directed
 Rear cases of serious burns have been reported with products of this type
 Do not bandage tightly or use with a heating pad
 Avoid contact with eyes and mucous membranes
 Do not apply to wounds or damaged skin.
 Do not use at the same time as other topical analgesics.

Stop use and ask a doctor if:

 Condition worsens
 Redness is present
 Irritation develops
 Symptoms persist for more than 7 days or clear up and occur again within a few days
 You experience signs of skin injury, such as pain, swelling or blistering where the product was applied.
If pregnant or breastfeeding, ask a health professional before use.

KEEP OUT OF REACH OF CHILDREN

If swallowed, get medical help or contact a Poison Control Center 800-222-1222 right away.

Directions

For use by adults and children 12 years of age and older:
 Carefully remove backing from patch
 Apply sticky side of patch to affected area.
 Wear 1 patch up to 8 hours. Repeat as necessary, but no more than 3 times daily.
 Discard patch after single use.
 Reseal pouch after opening.
Children under 12 years of age: consult a physician.

STORAGE AND HANDLING

Store between 15-30℃(59-86℉) keep away from children

Inactive ingredients

Glycerin, Polyacrylic acid, Polysorbate 80, Polyvinyl alcohol, Propylene glycol, Dihydroxyaluminum aminoacetate, DMDM hydantoin, Isopropyl myristate, Edetic acid, Sodium polyacrylate, Tartaric acid, Titanium dioxide, Water